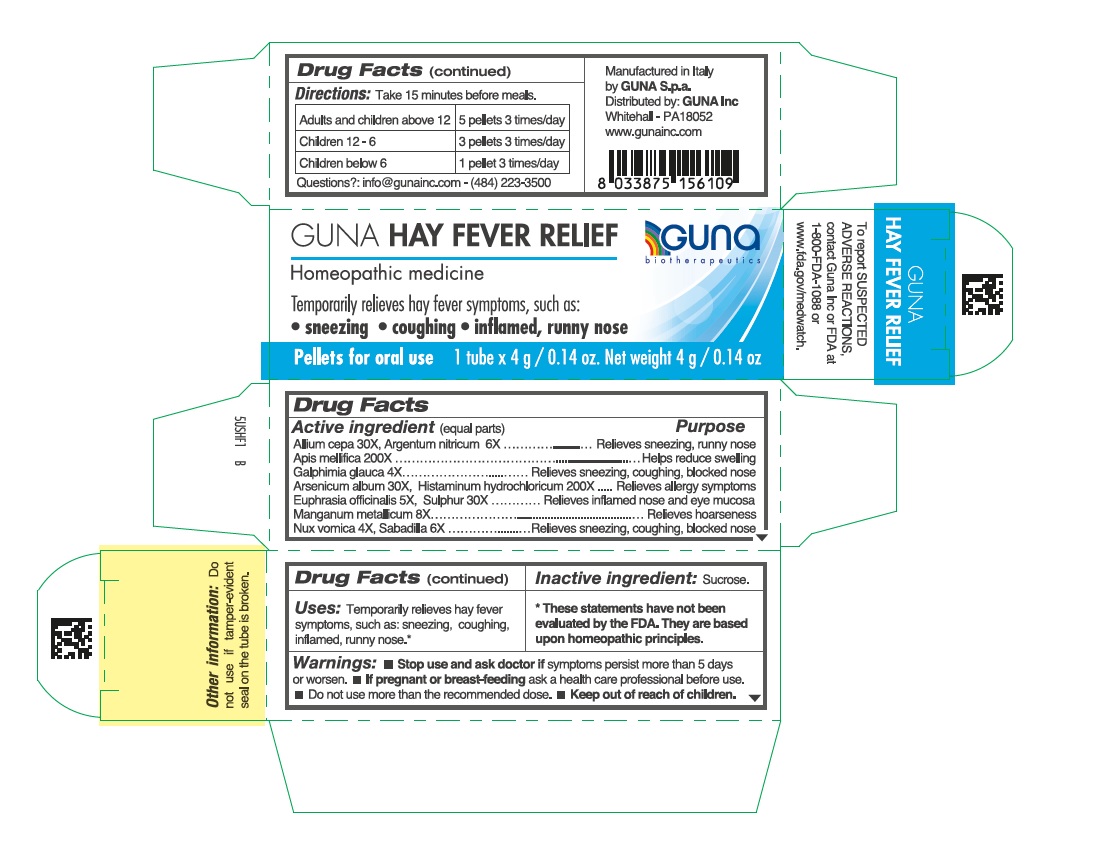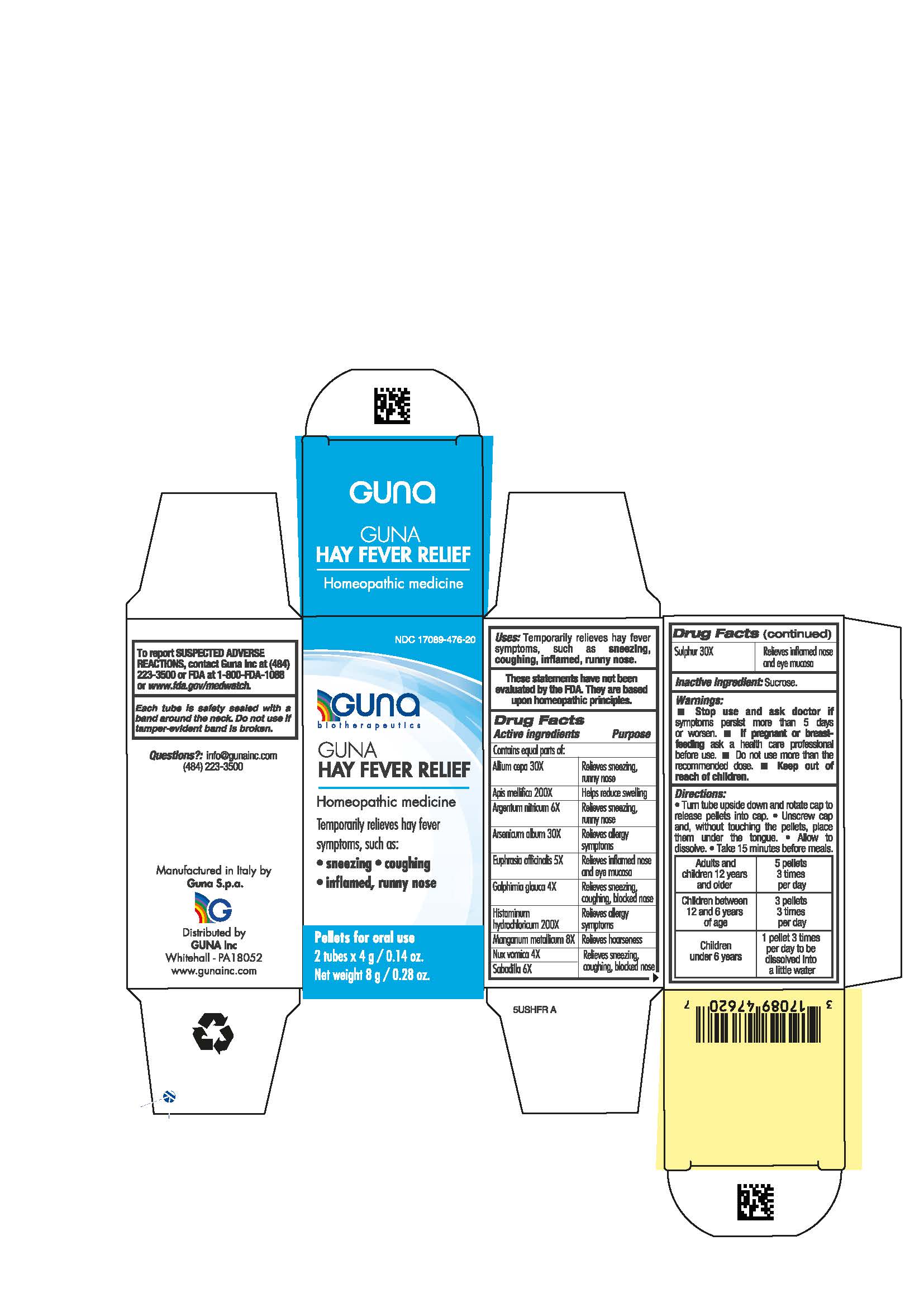 DRUG LABEL: GUNA HAY FEVER RELIEF
NDC: 17089-476 | Form: PELLET
Manufacturer: Guna spa
Category: homeopathic | Type: HUMAN OTC DRUG LABEL
Date: 20211215

ACTIVE INGREDIENTS: STRYCHNOS NUX-VOMICA SEED 4 [hp_X]/4 g; HISTAMINE DIHYDROCHLORIDE 200 [hp_X]/4 g; MANGANESE 8 [hp_X]/4 g; SCHOENOCAULON OFFICINALE SEED 6 [hp_X]/4 g; ONION 30 [hp_X]/4 g; APIS MELLIFERA 200 [hp_X]/4 g; SILVER NITRATE 6 [hp_X]/4 g; EUPHRASIA STRICTA 5 [hp_X]/4 g; GALPHIMIA GLAUCA FLOWERING TOP 4 [hp_X]/4 g; SULFUR 30 [hp_X]/4 g; ARSENIC TRIOXIDE 30 [hp_X]/4 g
INACTIVE INGREDIENTS: SUCROSE 4 g/4 g

GUNA HAY FEVER RELIEF

INDICATIONS AND USAGE

Temporarily relieves hay fever symptoms, such as:

● sneezing

● coughing

● inflamed, runny nose

QUESTIONS

info@gunainc.com
(484) 223-3500

WARNINGS

Keep out of reach of children

PREGNANCY

If pregnant or breast-feeding ask a health care professional before use.

USES

Temporarily relieves hay fever symptoms, such as:

● sneezing

● coughing

● inflamed, runny nose

WARNINGS

- Stop use and ask doctor if symptoms persist more than 5 days or worsen.
- If pregnant or breast-feeding ask a health care professional before use
- keep out of reach of children

- Stop use and ask doctor if symptoms persist more than 5 days or worsen.
- If pregnant or breast-feeding ask a health professional before use.
- Do not use more than the recommended dose.
- Keep out of reach of children.

ACTIVE INGREDIENTS/PURPOSE

Allium cepa 30X Relieves sneezing, runny nose

Apis mellifica 200X Helps reduce swelling

Galphimia glauca 4X Relieves sneezing, coughing, blocked nose

Argentum nitricum 6X Relieves sneezing, runny nose

Arsenicum album 30X Relieves allergy symptoms

Euphrasia officinalis 5X Relieves inflamed nose and eye mucosa

Histaminum hydrochloricum 200X Relieves allergy symptoms

Manganum metallicum 8X Relieves hoarseness

Nux vomica 4X Relieves sneezing, coughing, blocked nose

Sabadilla 6X Relieves sneezing, coughing, blocked nose

Sulphur 30X Relieves inflamed nose and eye mucosa

DIRECTIONS

- Turn tube upside down and rotate cap to release pellets into cap. ● Unscrew cap and, without touching the pellets, place them under the tongue. ● Allow to dissolve. ● Take 15 minutes before meals.

DOSAGE AND ADMINISTRATION

- Adults and children 12 years and older 5 pellets 3 times per day
- Children between 12 and 6 years of age 3 pellets 3 times per day
- Children under 6 years 1 pellet 3 times per day to be disoolved into a little water

Inactive ingredient: Sucrose.

- Keep out of reach of children